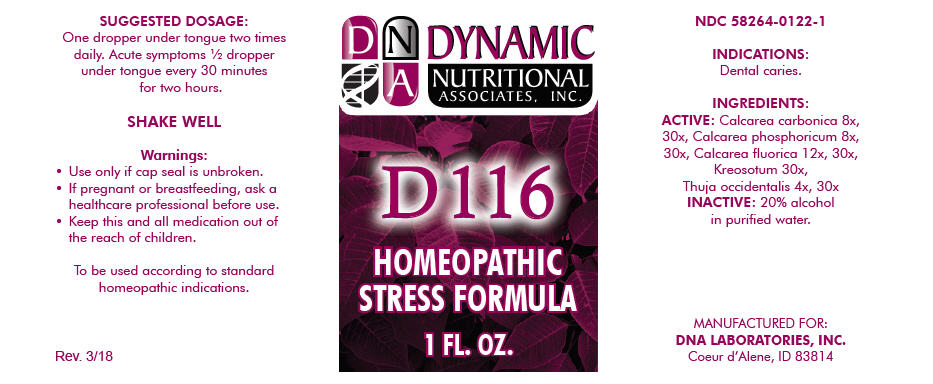 DRUG LABEL: D-116
NDC: 58264-0122 | Form: SOLUTION
Manufacturer: DNA Labs, Inc.
Category: homeopathic | Type: HUMAN OTC DRUG LABEL
Date: 20250113

ACTIVE INGREDIENTS: OYSTER SHELL CALCIUM CARBONATE, CRUDE 8 [hp_X]/1 mL; TRIBASIC CALCIUM PHOSPHATE 8 [hp_X]/1 mL; CALCIUM FLUORIDE 12 [hp_X]/1 mL; WOOD CREOSOTE 30 [hp_X]/1 mL; THUJA OCCIDENTALIS LEAFY TWIG 4 [hp_X]/1 mL
INACTIVE INGREDIENTS: ALCOHOL; WATER

D-116

NDC 58264-0122-1

INDICATIONS

PURPOSE

Dental caries.

INGREDIENTS

ACTIVE

Calcarea carbonica 8x, 30x, Calcarea phosphoricum 8x, 30x, Calcarea fluorica 12x, 30x, Kreosotum 30x, Thuja occidentalis 4x, 30x

INACTIVE

20% alcohol in purified water.

SUGGESTED DOSAGE

One dropper under tongue two times daily. Acute symptoms ½ dropper under tongue every 30 minutes for two hours.

STORAGE AND HANDLING

SHAKE WELL

Warnings

- Use only if cap seal is unbroken.

PREGNANCY OR BREAST FEEDING

- If pregnant or breastfeeding, ask a healthcare professional before use.

KEEP OUT OF REACH OF CHILDREN

- Keep this and all medication out of the reach of children.

To be used according to standard homeopathic indications.

PRINCIPAL DISPLAY PANEL - 1 FL. OZ. Bottle Label

DYNAMIC
NUTRITIONAL
ASSOCIATES, INC.

D 116

HOMEOPATHIC
STRESS FORMULA

1 FL. OZ.